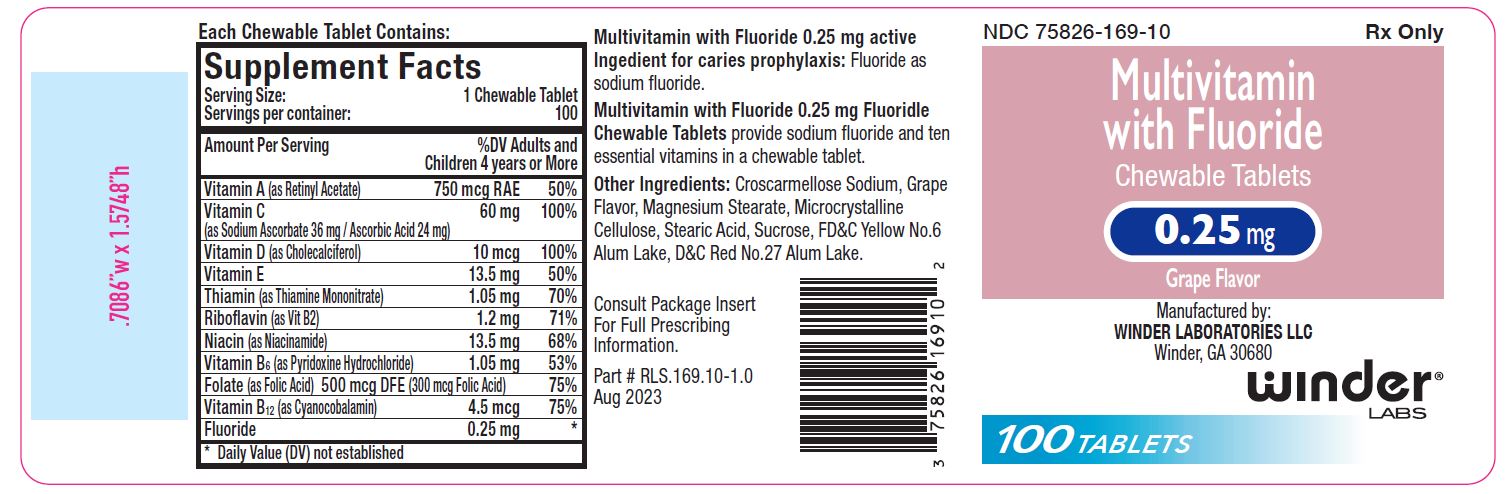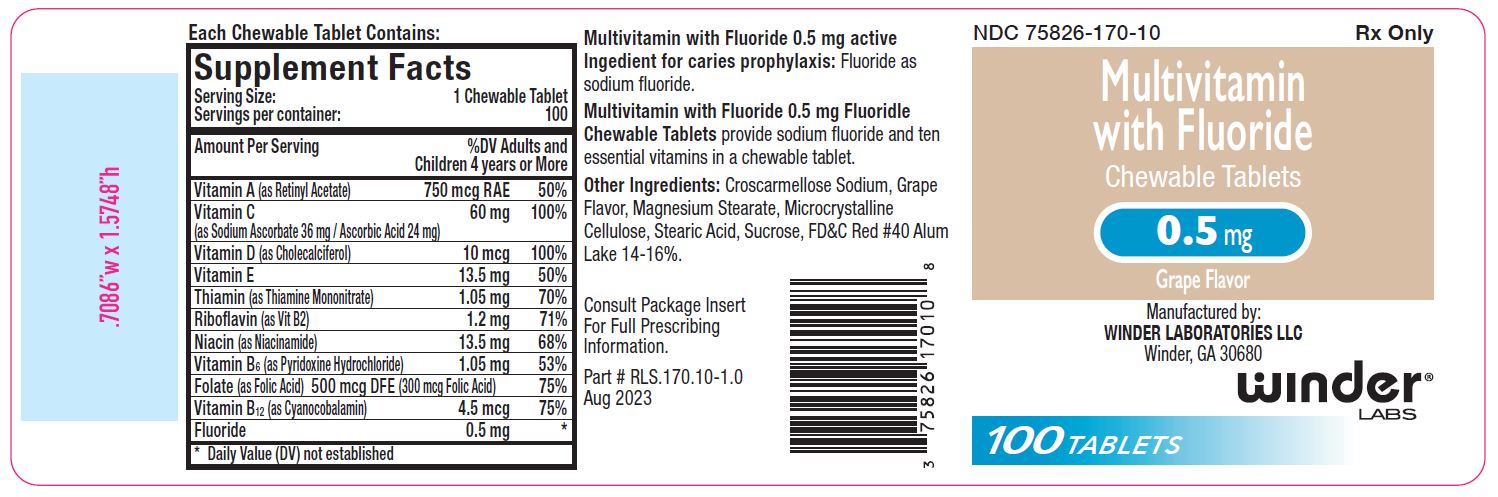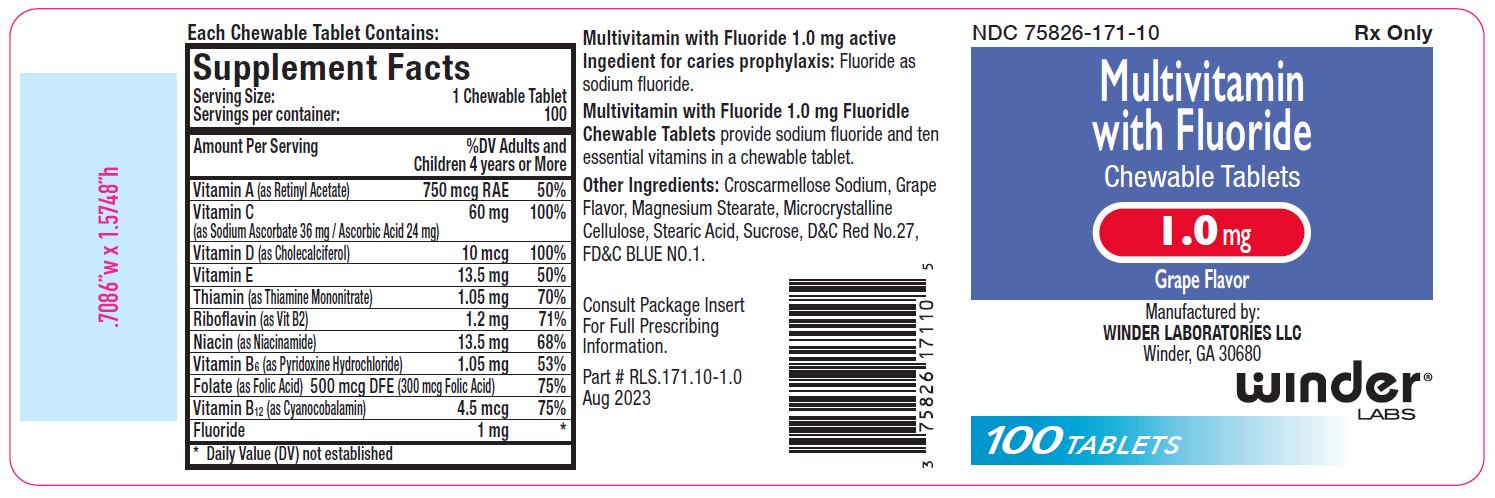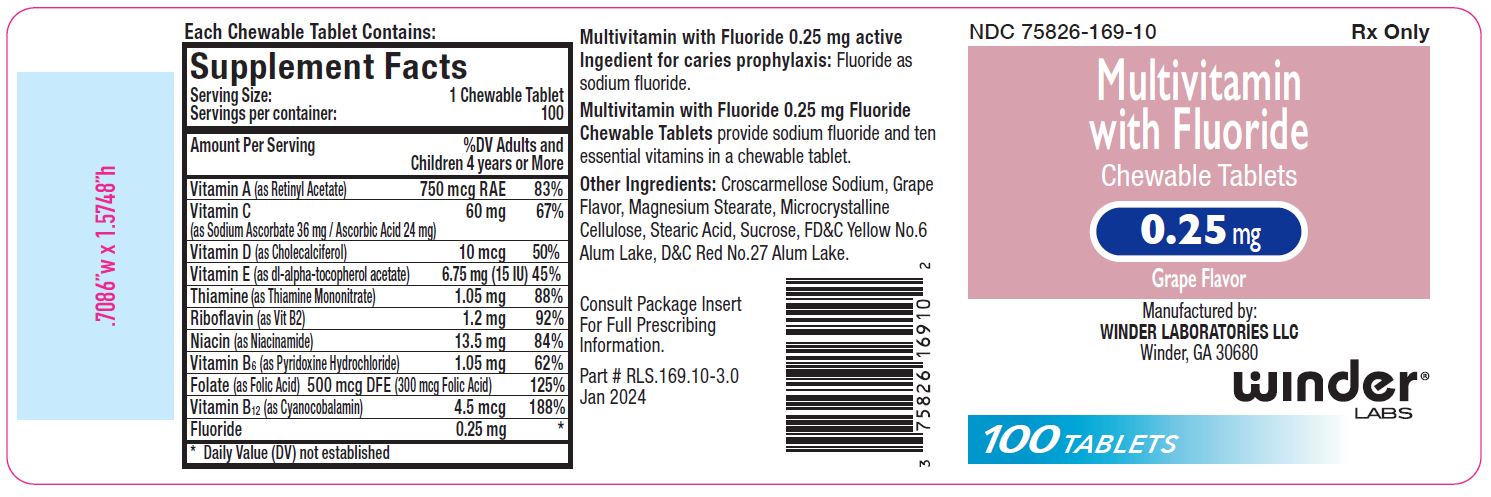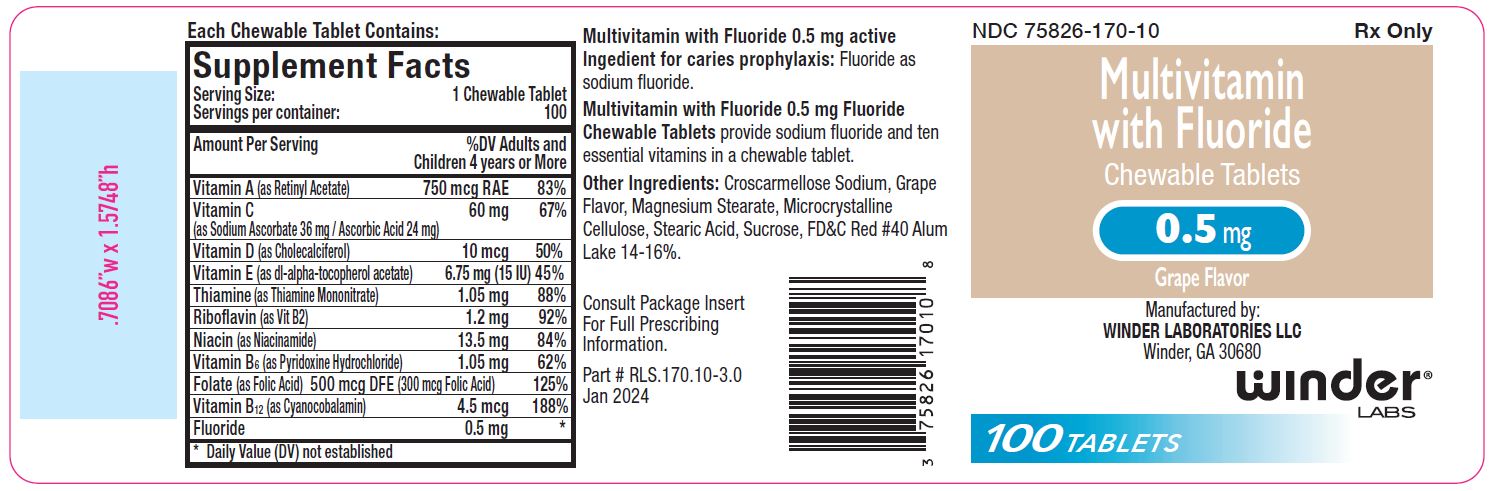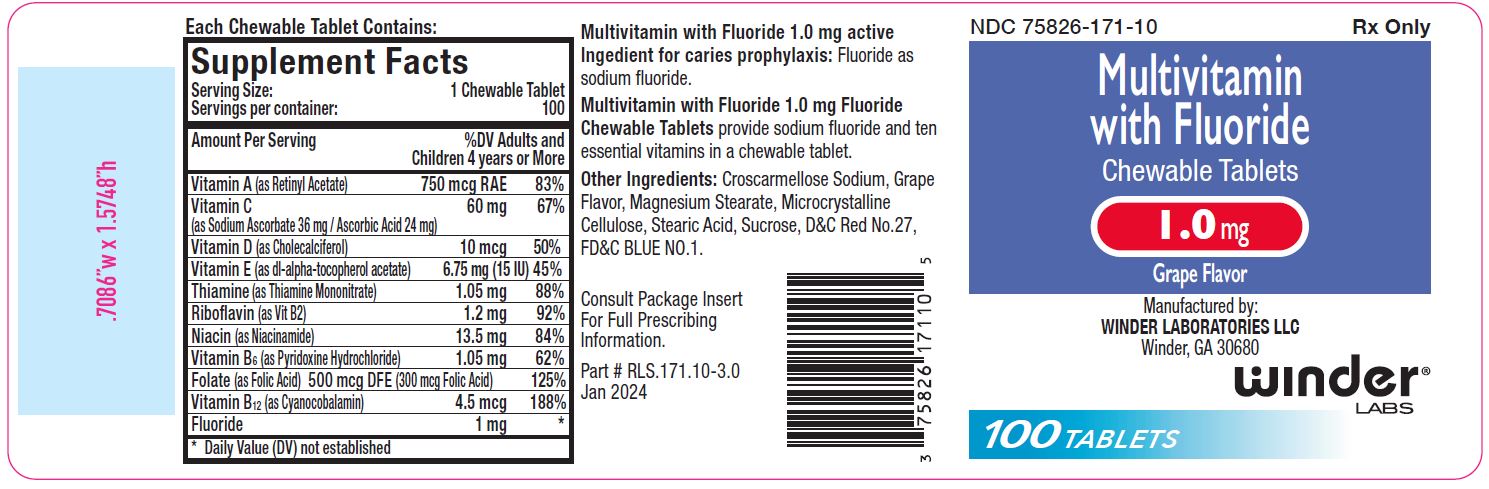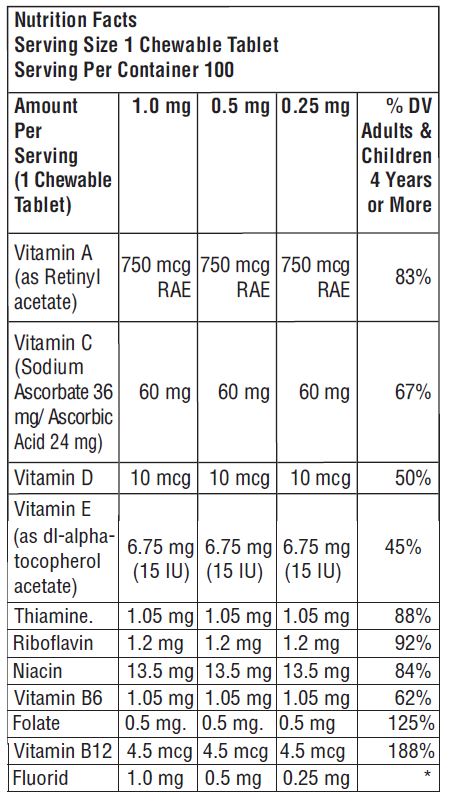 DRUG LABEL: Multivitamin with Fluoride
NDC: 75826-170 | Form: TABLET, CHEWABLE
Manufacturer: WINDER LABORATORIES, LLC
Category: prescription | Type: HUMAN PRESCRIPTION DRUG LABEL
Date: 20250827

ACTIVE INGREDIENTS: SODIUM FLUORIDE 0.5 mg/1 1; VITAMIN A 750 ug/1 1; ASCORBIC ACID 24 mg/1 1; SODIUM ASCORBATE 36 mg/1 1; CHOLECALCIFEROL 10 ug/1 1; .ALPHA.-TOCOPHEROL ACETATE, DL- 6.75 mg/1 1; THIAMINE MONONITRATE 1.05 mg/1 1; RIBOFLAVIN 1.2 mg/1 1; NIACINAMIDE 13.5 mg/1 1; PYRIDOXINE HYDROCHLORIDE 1.05 mg/1 1; FOLIC ACID 500 ug/1 1; CYANOCOBALAMIN 4.5 ug/1 1
INACTIVE INGREDIENTS: SUCROSE; CROSCARMELLOSE SODIUM; FD&C RED NO. 40; MAGNESIUM STEARATE; MICROCRYSTALLINE CELLULOSE 102; STEARIC ACID

MULTIVITAMIN WITH FLUORIDE CHEWABLE TABLETS
0.25 mg, 0.5 mg and 1.0 mg
Prescribing Information

Rx Only

* Daily Value (% DV) not established

Active ingredients:
Fluoride as sodium fluoride.
Other Ingredients:
Croscarmellose Sodium, Grape Flavor, Magnesium Stearate, Microcrystalline Cellulose, Stearic Acid, Sucrose.
0.25 mg also contains: D&C Red #27 Alum Lake and FD&C Yellow #6 Alum Lake.
0.5 mg also contains: FD&C Red #40 Alum Lake.
1.0 mg also contains: D&C Red #27 and FD&C Blue #1.

CLINICAL PHARMACOLOGY

It is well established that fluoridation of the water supply (1 ppm fluoride) during the period of tooth development leads to a significant decrease in the incidence of dental caries.

Multivitamin with Fluoride Chewable Tabletsprovide sodium fluoride and ten essential vitamins in a chewable tablet. Because the tablets are chewable, they provide a topical as well as systemic source of fluoride.
Hydroxyapatite is the principal crystal for all calcified tissue in the human body. The fluoride ion reacts with the hydroxyapatite in the tooth as it is formed to produce the more caries-resistant crystal, fluorapatite. The reaction may be expressed by the equation:

Ca 10 (PO 4) 6(OH) 2+ 2F -------› Ca 10(PO 4)F 2+ 2OH -
(Hydroxyapatite) (Fluorapatite)

(Hydroxyapatite) (Fluorapatite)

Three stages of fluoride deposition in tooth enamel can be distinguished:

1. Small amounts (reflecting the low levels of fluoride in tissue fluids) are incorporated into the enamel crystals while they are being formed.
2. After enamel has been laid down, fluoride deposition continues in the surface enamel. Diffusion of fluoride from the surface inward is apparently restricted.
3. After eruption, the surface enamel acquires fluoride from the water, food, supplementary fluoride and smaller amounts from saliva.

INDICATIONS AND USAGE

Supplementation of the diet with fluoride and ten essential vitamins.

Multivitamin with 1.0 mg Fluoride Chewable Tabletsprovide fluoride in tablet form for children 6-16 years of age in areas where the water fluoride level is less than 0.3 ppm.

Multivitamin with 0.5 mg Fluoride Chewable Tablets provide fluoride in tablet form for children 4-6 years of age where the water fluoride level is less than 0.3 ppm, and for children 6 years of age and above where the drinking water contains 0.3 through 0.6 ppm of fluoride.

Multivitamin with 0.25 mg Fluoride Chewable Tabletsprovide fluoride in tablet form for children 4-6 years of age where the drinking water contains 0.3 through 0.6 ppm of fluoride.

Multivitamin with Fluoride Chewable Tabletssupply significant amounts of vitamins A, C, D, E, thiamine, riboflavin, niacin, vitamin B6, vitamin B12, and folate to supplement the diet, and to help assure that nutritional deficiencies of these vitamins will not develop.
Thus, in a single easy-to-use preparation, children obtain ten essential vitamins and the important mineral, fluoride.
Supplementation of the diet with fluoride for caries prophylaxis.
The American Academy of Pediatrics recommends that children up to age 16, in areas where drinking water contains less than optimal levels of fluoride, receive daily fluoride supplementation.

Children using Multivitamin with Fluoride Chewable Tabletsregularly should receive semiannual dental examinations. The regular brushing of teeth and attention to good oral hygiene practices are also essential.

Multivitamin with Fluoride Chewable tabletsare prescription product for the clinical dietary management of metabolic processes of caries prophylaxis and provides supplementation of the diet with ten essential vitamins.

WARNING Keep this and all medication out of the reach of children. In case of accidental overdose, seek professional assistance or contact a poison control center immediately.

Keep this and all medication out of the reach of children. In case of accidental overdose, seek professional assistance or contact a poison control center immediately.

CAUTION
Should be chewed. This product, as with all chewable tablets, is not recommended for children under age 4 due to risk of choking.
Do not eat or drink dairy products within one hour of fluoride administration.

PRECAUTIONS

The suggested dose of Multivitamin with Fluoride Chewable Tabletsshould not be exceeded, since dental fluorosis may result from continued ingestion of large amounts of fluoride.
Before prescribing Multivitamin with Fluoride Chewable Tablets:

1. Determine the fluoride content of the drinking water from all major sources.
2. Make sure the child is not receiving significant amounts of fluoride from other sources such as medications and swallowed toothpaste.
3. Periodically check to make sure that the child does not develop significant dental fluorosis.

ADVERSE REACTIONS

Allergic rash and other idiosyncrasies have been rarely reported.

DOSAGE AND ADMINISTRATION

One tablet daily or as prescribed.

HOW SUPPLIED

3.25 mg: Multivitamin chewable tablets containing 0.25 mg fluoride are pink-colored, grape flavor, un-scored, round tablet, debossed with “WL” “169” on one side and plain on other side of tablet. Available in bottle of 100 (NDC 75826-169-10).
0.5 mg: Multivitamin chewable tablets containing 0.5 mg fluoride are peach-colored, grape flavor, un-scored, round tablet, debossed with “WL” “170” on one side and plain on other side of tablet. Available in bottle of 100 (NDC 75826-170-10).
1.0 mg: Multivitamin chewable tablets containing 1.0 mg fluoride are purple-colored, grape flavor, un-scored, round tablet, debossed with “WL” “171” on one side and plain on other side of tablet. Available in bottle of 100 (NDC 75826-171-10).

STORAGE
Store at 20° - 25°C (68°-77°F); excursions permitted to 15° - 30°C (59°-86°F). See USP Controlled Room Temperature.

Dispense in a tight, light resistant container with a child-resistant closure as defined in the USP/NF. All prescription substitutions using this product shall be pursuant to state statutes as applicable. This is not an Orange Book product.

Manufactured by:
Winder Laboratories LLC
Winder GA, 30680
RLS.170.99-3.0
Rev: 01/2024